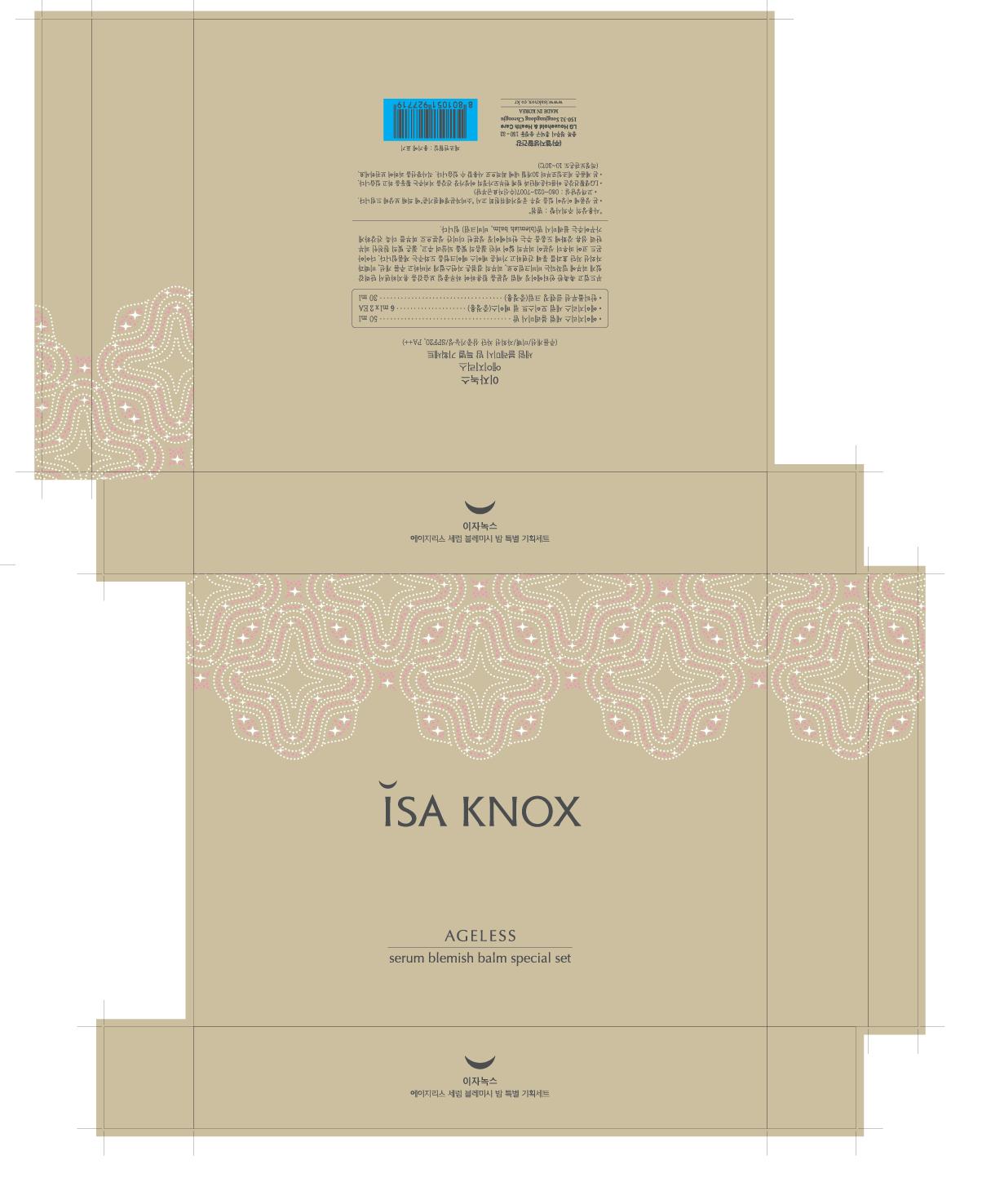 DRUG LABEL: ISAKNOX AGELESS SERUM BLEMISH BALM
NDC: 53208-475 | Form: CREAM
Manufacturer: LG Household and Healthcare, Inc. 
Category: otc | Type: HUMAN OTC DRUG LABEL
Date: 20120515

ACTIVE INGREDIENTS: TITANIUM DIOXIDE 5.76 mL/100 mL; OCTYLTRIETHOXYSILANE 0.12 mL/100 mL; ALUMINUM HYDROXIDE 0.12 mL/100 mL; ATRACTYLODES JAPONICA ROOT  0.05 mL/100 mL; OCTINOXATE 5 mL/100 mL
INACTIVE INGREDIENTS: WATER; ETHYLHEXYL PALMITATE; BUTYLENE GLYCOL; CYCLOMETHICONE 5; MEDIUM-CHAIN TRIGLYCERIDES; GLYCERIN; PARAFFIN; DIMETHICONE; MAGNESIUM SULFATE, UNSPECIFIED; SORBITAN OLIVATE; PHENOXYETHANOL; METHYLPARABEN; ETHYLPARABEN; PROPYLPARABEN

Drug Fact

Active Ingredients

Enter section text here

Warning and Precautions

For external use only.

Keep out of reach of children. Is swallowed, get medical help or contact a Poison Control Center right away.

WHEN USING

Keep out of eyes. Rinse with water to remove.

Package Label

Isaknox
Ageless

Blemish Balm